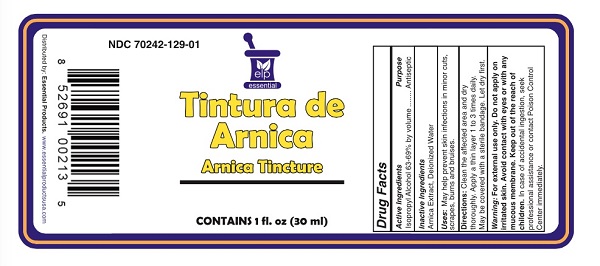 DRUG LABEL: Tintura de Arnica
NDC: 70242-129 | Form: SOLUTION
Manufacturer: Dannso Corp./d.b.a. Essential Products
Category: otc | Type: HUMAN OTC DRUG LABEL
Date: 20230101

ACTIVE INGREDIENTS: ISOPROPYL ALCOHOL 0.13 g/1 mL
INACTIVE INGREDIENTS: ARNICA MONTANA FLOWER; WATER

Arnica Tincture

Active Ingredients Purpose

Isopropyl Alcohol 63-69% by Volume................... Antiseptic

Use

May help prevent skin infection in

- minor cuts
- scrapes
- burns
- bruises

Keep out of reach of children. If swallowed, get medical help or contact a Poison Control Center right away.

INDICATIONS AND USAGE

Antiseptic

For External Use Only

Directions

- clean the affected area
- and dry thoroughly. Apply a thin layer 1 to 3 times daily.
- May be covered with a sterile bandage, let dry first.

Warnings For external use only

Avoid Contact with eyes.

When using this product

- do not use on irritated skin, in or near eyes or mocous membranes, on wounds or damaged skin, if prone to allergic reaction
- Fatal if swallowed.

Stop use and ask a doctor if condition persists or gets worse

INACTIVE INGREDIENT

Inactive Ingredients Arnica Extract, Isopropyl Alcohol, Deionized Water